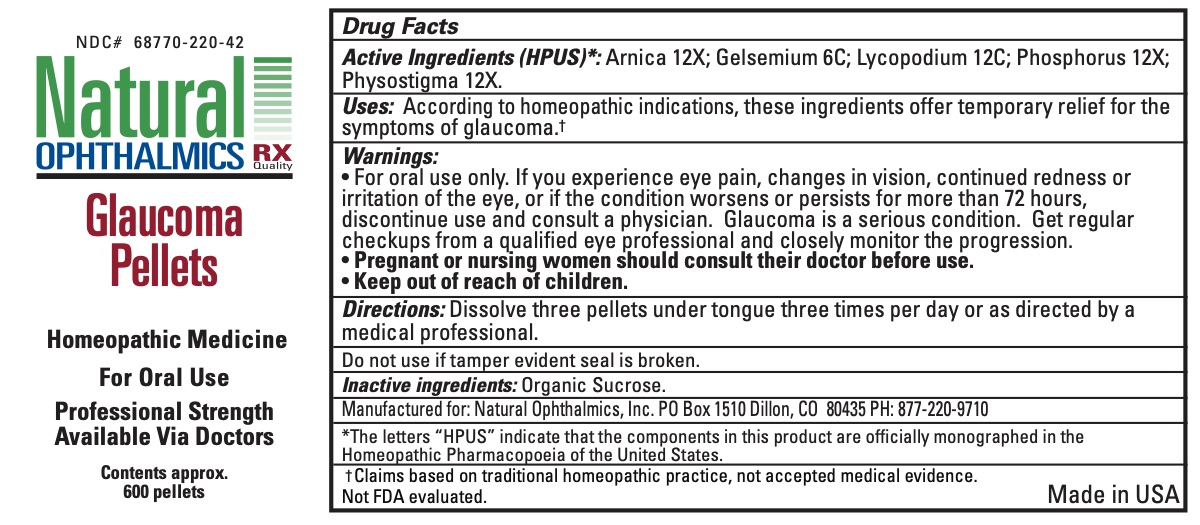 DRUG LABEL: Glaucoma
NDC: 68770-220 | Form: PELLET
Manufacturer: Natural Ophthalmics, Inc
Category: homeopathic | Type: HUMAN OTC DRUG LABEL
Date: 20231231

ACTIVE INGREDIENTS: ARNICA MONTANA 12 [hp_X]/1 1; GELSEMIUM SEMPERVIRENS ROOT 6 [hp_C]/1 1; LYCOPODIUM CLAVATUM SPORE 12 [hp_C]/1 1; PHYSOSTIGMA VENENOSUM SEED 12 [hp_X]/1 1; PHOSPHORUS 12 [hp_X]/1 1
INACTIVE INGREDIENTS: SUCROSE

Glaucoma Pellets

ACTIVE INGREDIENT

Active Ingredients (HPUS)*: Arnica 12X; Gelsemium 6C; Lycopodium 12C; Phosphorus 12X; Physostigma 12X.

INDICATIONS AND USAGE

Uses: According to homeopathic indications, these ingredients offer temporary relief for the symptoms of glaucoma.†

Warnings:

• For oral use only. If you experience eye pain, changes in vision, continued redness or irritation of the eye, or if the condition worsens or persists for more than 72 hours, discontinue use and consult a physician. Glaucoma is a serious condition. Get regular checkups from a qualified eye professional and closely monitor the progression.

PREGNANCY OR BREAST FEEDING

Pregnant or nursing women should consult their doctor before use.

Keep out of reach of children

INACTIVE INGREDIENT

organic sucrose

Directions:

Dissolve three pellets under tongue three times per day or as directed by a medical professional.

Do not use if tamper evident seal is broken.

*The letters “HPUS” indicate that the components in this product are officially monographed in the Homeopathic Pharmacopoeia of the United States.

† Claims based on traditional homeopathic practice, not accepted medical evidence.
Not FDA evaluated.

Manufactured for: Natural Ophthalmics, Inc. PO Box 1510 Dillon, CO 80435 PH: 877-220-9710